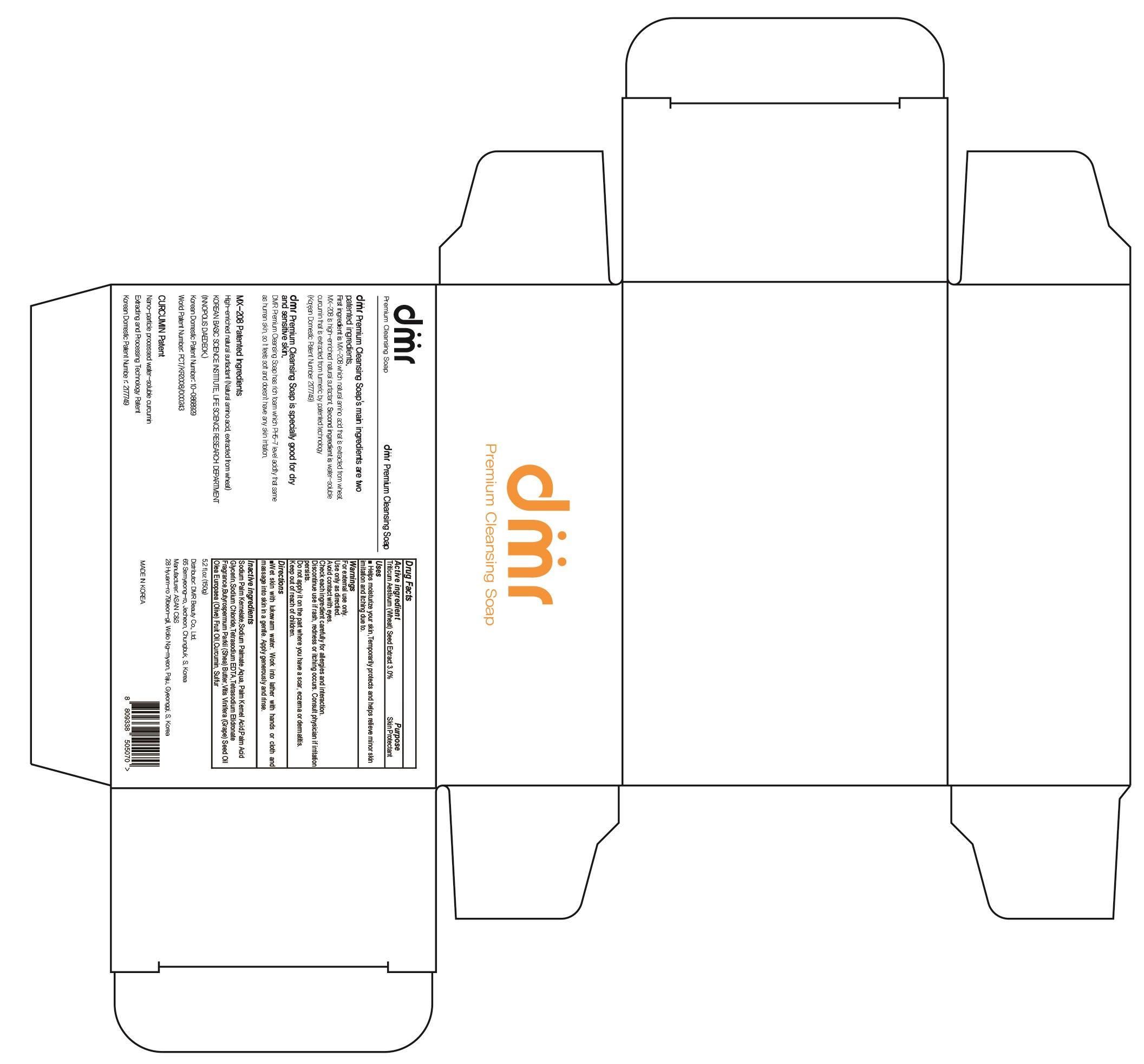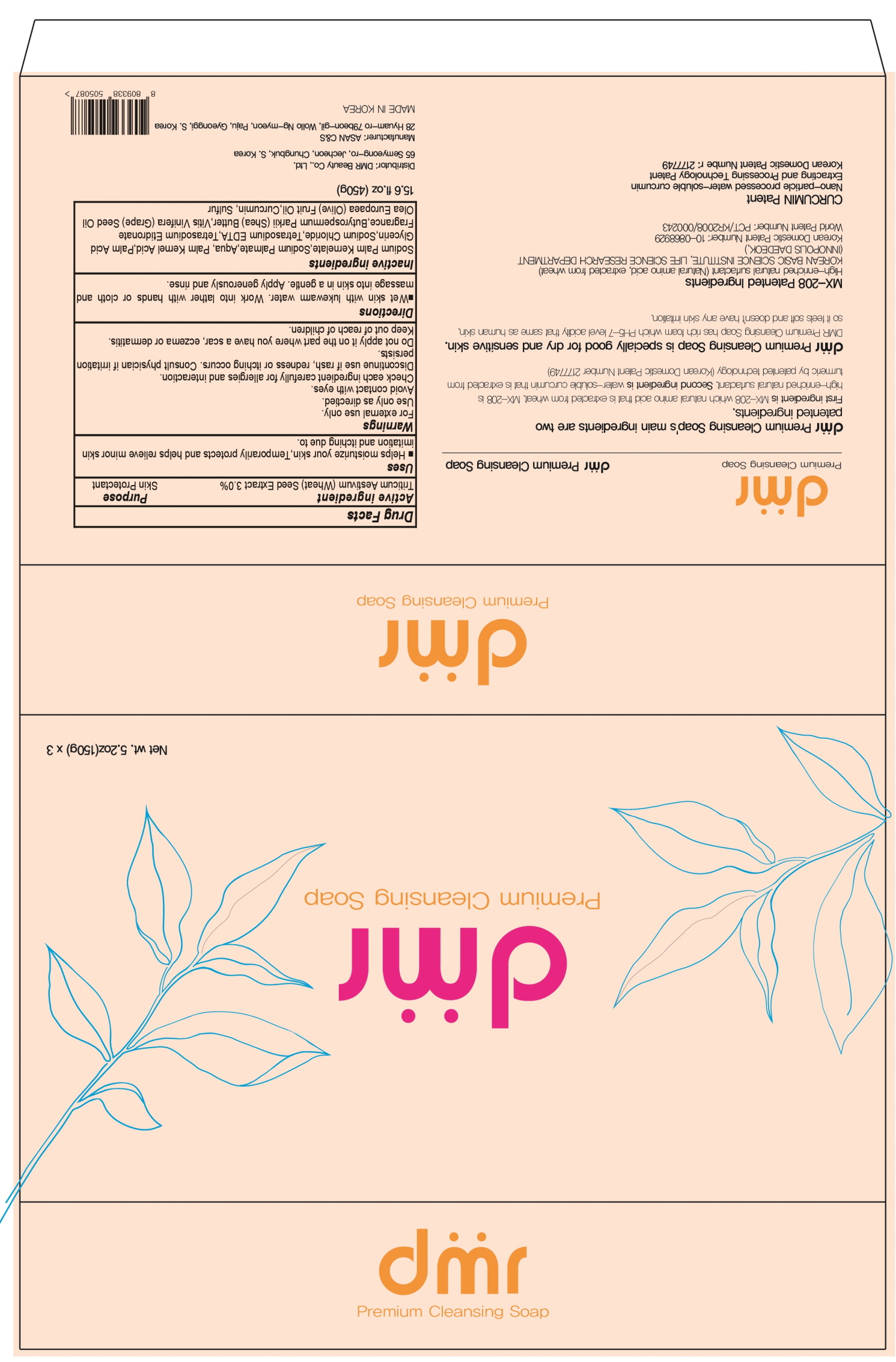 DRUG LABEL: DMR Premium Cleansing
NDC: 82629-010 | Form: SOAP
Manufacturer: DMR Beauty Co., Ltd.
Category: otc | Type: HUMAN OTC DRUG LABEL
Date: 20220531

ACTIVE INGREDIENTS: WHEAT 3.0 g/100 g
INACTIVE INGREDIENTS: SODIUM PALM KERNELATE; Sodium Palmate; WATER

ACTIVE INGREDIENT

Triticum Aestivum (Wheat) Seed Extract 3.0%

INACTIVE INGREDIENTS

Sodium Palm Kernelate,Sodium Palmate,Aqua, Palm Kernel Acid,Palm Acid Glycerin,Sodium Chloride,Tetrasodium EDTA,Tetrasodium Etidronate
Fragrance,Butyrospermum Parkii (Shea) Butter,Vitis Vinifera (Grape) Seed Oil, Olea Europaea (Olive) Fruit Oil,Curcumin, Sulfur

PURPOSE

Skin Protectant

WARNINGS

For external use only.
Use only as directied.
Avoid contact with eyes.
Check each ingredient carefully for allergies and interaction.
Discontinue use if rash, redness or itching occurs. Consult physician if irritation persists.
Do not apply it on the part where you have a scar, eczema or dermatitis.
Keep out of reach of children.

KEEP OUT OF REACH OF CHILDREN

Uses

■ Helps moisturize your skin,Temporarily protects and helps relieve minor skin imitation and itching due to.

Directions

■Wet skin with lukewarm water. Work into lather with hands or cloth and massage into skin in a gentle. Apply generously and rinse.